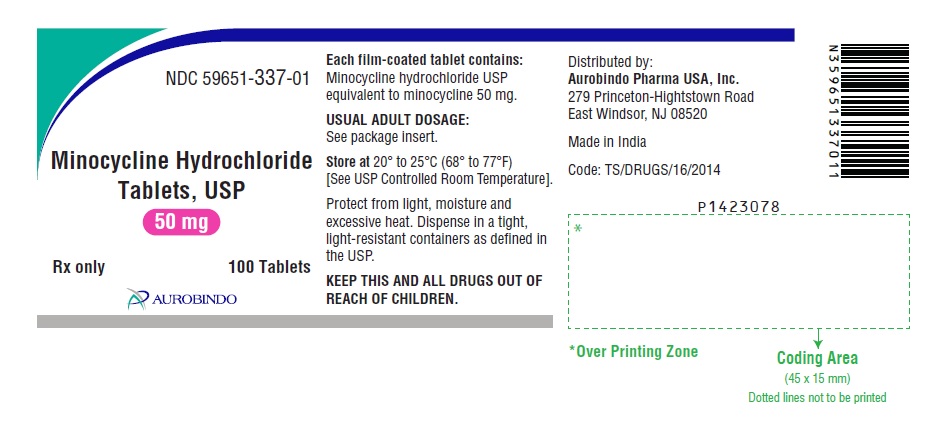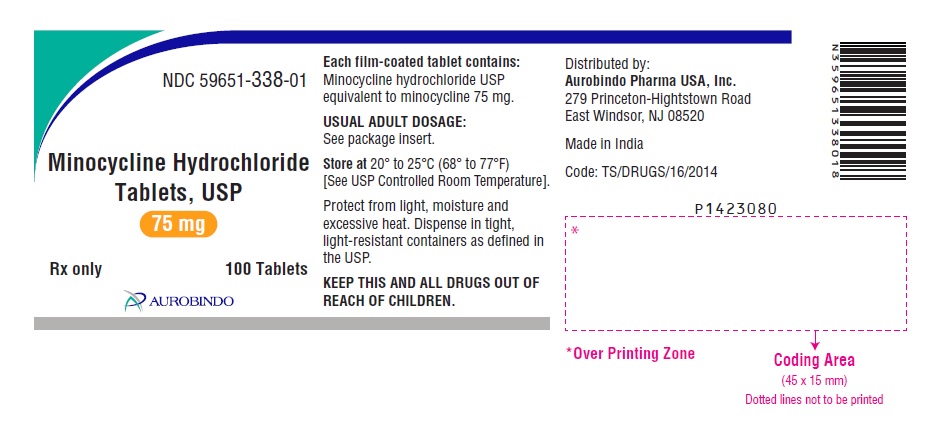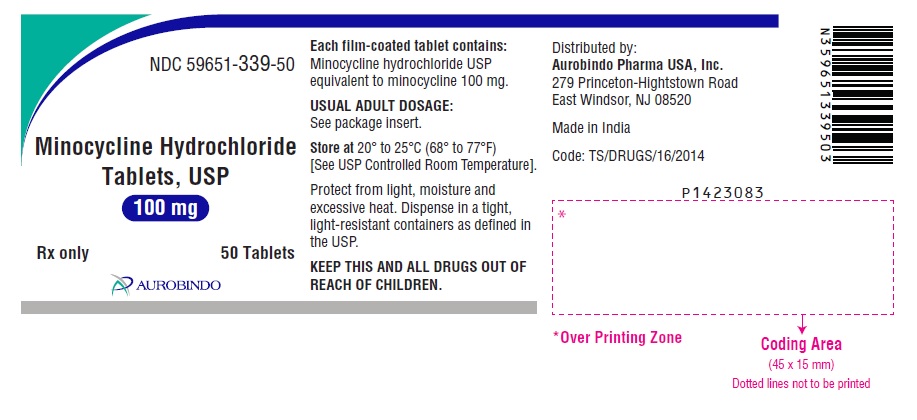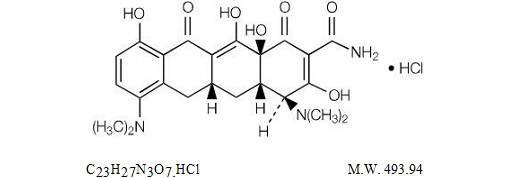 DRUG LABEL: Minocycline Hydrochloride
NDC: 59651-337 | Form: TABLET, FILM COATED
Manufacturer: Aurobindo Pharma Limited
Category: prescription | Type: Human Prescription Drug Label
Date: 20250101

ACTIVE INGREDIENTS: MINOCYCLINE HYDROCHLORIDE 50 mg/1 1
INACTIVE INGREDIENTS: SILICON DIOXIDE; HYPROMELLOSE 2910 (6 MPA.S); LACTOSE MONOHYDRATE; MAGNESIUM STEARATE; MICROCRYSTALLINE CELLULOSE 101; MICROCRYSTALLINE CELLULOSE 102; POLYETHYLENE GLYCOL 400; POLYSORBATE 80; POVIDONE K30; SODIUM STARCH GLYCOLATE TYPE A POTATO; TITANIUM DIOXIDE

Minocycline Hydrochloride Tablets, USP
Rx only

MICROBIOLOGY

To reduce the development of drug-resistant bacteria and maintain the effectiveness of minocycline hydrochloride tablets and other antibacterial drugs, minocycline hydrochloride tablets should be used only to treat or prevent infections that are proven or strongly suspected to be caused by bacteria.

DESCRIPTION

Minocycline hydrochloride, is a semisynthetic derivative of tetracycline, 4,7-Bis(dimethylamino)-1,4,4a,5,5a,6,11,12a-octahydro-3,10,12,12a-tetrahydroxy-1,11-dioxo-2-naphthacenecarboxamide monohydrochloride. Its structural formula is:

Minocycline hydrochloride tablets, USP for oral administration contain minocycline hydrochloride USP equivalent to 50 mg, 75 mg or 100 mg of minocycline. In addition, 50 mg, 75 mg and 100 mg tablets contain the following inactive ingredients: colloidal silicon dioxide, hypromellose, lactose monohydrate, magnesium stearate, microcrystalline cellulose, polyethylene glycol, polysorbate 80, povidone, sodium starch glycolate and titanium dioxide.

CLINICAL PHARMACOLOGY

Following a single dose of one 100 mg tablet of minocycline hydrochloride administered to 28 normal fasting adult volunteers, maximum serum concentrations were attained in 1 to 3 hours (average 1.71 hours) and ranged from 491.71 to 1292.70 ng/mL (average 758.29 ng/mL). The serum half-life in the normal volunteers ranged from 11.38 to 24.31 hours (average 17.03 hours).

When minocycline hydrochloride tablets were given concomitantly with a meal, which included dairy products, the extent of absorption of minocycline hydrochloride tablets was slightly decreased (6%). The peak plasma concentrations were slightly decreased (12%) and delayed by 1.09 hours when administered with food, compared to dosing under fasting conditions. Minocycline hydrochloride may be administered with or without food.

In previous studies with other minocycline dosage forms, the minocycline serum half-life ranged from 11 to 16 hours in 7 patients with hepatic dysfunction, and from 18 to 69 hours in 5 patients with renal dysfunction. The urinary and fecal recovery of minocycline when administered to 12 normal volunteers was one-half to one-third that of other tetracyclines.

Microbiology

The tetracyclines are primarily bacteriostatic and are thought to exert their antimicrobial effect by the inhibition of protein synthesis. The tetracyclines, including minocycline, have similar antimicrobial spectra of activity against a wide range of gram-positive and gram-negative organisms. Cross-resistance of these organisms to tetracycline is common.

Minocycline has been shown to be active against most strains of the following microorganisms, both in vitro and in clinical infections as described in the INDICATIONS AND USAGE section:

AEROBIC GRAM-POSITIVE MICROORGANISMS

Because many strains of the following gram-positive microorganisms have been shown to be resistant to tetracyclines, culture and susceptibility testing are especially recommended. Tetracycline antibiotics should not be used for streptococcal diseases unless the organism has been demonstrated to be susceptible. Tetracyclines are not the drug of choice in the treatment of any type of staphylococcal infection.

Bacillus anthracis a

Listeria monocytogenesa

Staphylococcus aureus

Streptococcus pneumoniae

AEROBIC GRAM-NEGATIVE MICROORGANISMS

Bartonella bacilliformis

Brucella species

Calymmatobacterium granulomatis

Campylobacter fetus

Francisella tularensis

Haemophilus ducreyi

Vibrio cholerae

Yersinia pestis

Because many strains of the following groups of gram-negative microorganisms have been shown to be resistant to tetracyclines, culture and susceptibility tests are especially recommended.

Acinetobacter species

Enterobacter aerogenes

Escherichia coli

Haemophilus influenzae

Klebsiella species

Neisseria gonorrhoeaea

Neisseria meningitidisa

Shigella species

“OTHER” MICROORGANISMS

Actinomyces species a

Borrelia recurrentis

Chlamydia psittaci

Chlamydia trachomatis

Clostridium speciesa

Entamoeba species

Fusobacterium nucleatum subspecies fusiforme a

Mycobacterium marinum

Mycoplasma pneumoniae

Propionibacterium acnes

Rickettsiae

Treponema pallidum subspecies palliduma

Treponema pallidum subspecies pertenuea

Ureaplasma urealyticum

a. When penicillin is contraindicated, tetracyclines are alternative drugs in the treatment of infections caused by the cited microorganisms.

Susceptibility Testing

For specific information regarding susceptibility test interpretive criteria and associated test methods and quality control standards recognized by FDA for this drug, please see: https://www.fda.gov/STIC.

INDICATIONS AND USAGE

Minocycline hydrochloride tablets are indicated in the treatment of the following infections due to susceptible strains of the designated microorganisms:

- Rocky Mountain spotted fever, typhus fever and the typhus group, Q fever, rickettsialpox and tick fevers caused by Rickettsiae.
- Respiratory tract infections caused by Mycoplasma pneumoniae.
- Lymphogranuloma venereum caused by Chlamydia trachomatis.
- Psittacosis (Ornithosis) due to Chlamydia psittaci.
- Trachoma caused by Chlamydia trachomatis, although the infectious agent is not always eliminated, as judged by immunofluorescence.
- Inclusion conjunctivitis caused by Chlamydia trachomatis.
- Nongonococcal urethritis, endocervical, or rectal infections in adults caused by Ureaplasma urealyticum or Chlamydia trachomatis.
- Relapsing fever due to Borrelia recurrentis.
- Chancroid caused by Haemophilus ducreyi
- Plague due to Yersinia pestis.
- Tularemia due to Francisella tularensis.
- Cholera caused by Vibrio cholerae.
- Campylobacter fetus infections caused by Campylobacter fetus.
- Brucellosis due to Brucella species (in conjunction with streptomycin).
- Bartonellosis due to Bartonella bacilliformis.
- Granuloma inguinale caused by Calymmatobacterium granulomatis.

Minocycline is indicated for treatment of infections caused by the following gram-negative microorganisms when bacteriologic testing indicates appropriate susceptibility to the drug:

- Escherichia coli.
- Enterobacter aerogenes.
- Shigella species.
- Acinetobacter species.
- Respiratory tract infection caused by Haemophilus influenzae.
- Respiratory tract and urinary tract infections caused by Klebsiella species.

Minocycline hydrochloride tablets are indicated for the treatment of infections caused by the following gram-positive microorganisms when bacteriologic testing indicates appropriate susceptibility to the drug:

- Upper respiratory tract infections caused by Streptococcus pneumoniae
- Skin and skin structure infections caused by Staphylococcus aureus. (Note: Minocycline is not the drug of choice in the treatment of any type of staphylococcal infection.)

When penicillin is contraindicated, minocycline is an alternative drug in the treatment of the following infections:

- Uncomplicated urethritis in men due to Neisseria gonorrhoeae and for the treatment of other gonococcal infections.
- Infections in women caused by Neisseria gonorrhoeae.
- Syphilis caused by Treponema pallidum subspecies pallidum.
- Yaws caused by Treponema pallidum subspecies pertenue.
- Listeriosis due to Listeria monocytogenes.
- Anthrax due to Bacillus anthracis.
- Vincent’s infection caused by Fusobacterium fusiforme.
- Actinomycosis caused by Actinomyces israelii.
- Infections caused by Clostridium species.

In acute intestinal amebiasis, minocycline may be a useful adjunct to amebicides.

In severe acne, minocycline may be useful adjunctive therapy.

Oral minocycline is indicated in the treatment of asymptomatic carriers of Neisseria meningitidis to eliminate the meningococci from the nasopharynx. In order to preserve the usefulness of minocycline in the treatment of asymptomatic meningococcal carriers, diagnostic laboratory procedures, including serotyping and susceptibility testing, should be performed to establish the carrier state and the correct treatment. It is recommended that the prophylactic use of minocycline be reserved for situations in which the risk of meningococcal meningitis is high.

Oral minocycline is not indicated for the treatment of meningococcal infection.

Although no controlled clinical efficacy studies have been conducted, limited clinical data show that oral minocycline hydrochloride has been used successfully in the treatment of infections caused by Mycobacterium marinum.

To reduce the development of drug-resistant bacteria and maintain the effectiveness of minocycline hydrochloride tablets and other antibacterial drugs, minocycline hydrochloride tablets should be used only to treat or prevent infections that are proven or strongly suspected to be caused by susceptible bacteria. When culture and susceptibility information are available, they should be considered in selecting or modifying antibacterial therapy. In the absence of such data, local epidemiology and susceptibility patterns may contribute to the empiric selection of therapy.

CONTRAINDICATIONS

This drug is contraindicated in persons who have shown hypersensitivity to any of the tetracyclines or to any of the components of the product formulation.

WARNINGS

MINOCYCLINE HYDROCHLORIDE TABLETS, LIKE OTHER TETRACYCLINE- CLASS ANTIBIOTICS, CAN CAUSE FETAL HARM WHEN ADMINISTERED TO A PREGNANT WOMAN. IF ANY TETRACYCLINE IS USED DURING PREGNANCY OR IF THE PATIENT BECOMES PREGNANT WHILE TAKING THESE DRUGS, THE PATIENT SHOULD BE APPRISED OF THE POTENTIAL HAZARD TO THE FETUS. THE USE OF DRUGS OF THE TETRACYCLINE CLASS DURING TOOTH DEVELOPMENT (LAST HALF OF PREGNANCY, INFANCY, AND CHILDHOOD TO THE AGE OF 8 YEARS) MAY CAUSE PERMANENT DISCOLORATION OF THE TEETH (YELLOW-GRAY-BROWN).

This adverse reaction is more common during long-term use of the drug but has been observed following repeated short-term courses. Enamel hypoplasia has also been reported. TETRACYCLINE DRUGS, THEREFORE, SHOULD NOT BE USED DURING TOOTH DEVELOPMENT UNLESS OTHER DRUGS ARE NOT LIKELY TO BE EFFECTIVE OR ARE CONTRAINDICATED.

All tetracyclines form a stable calcium complex in any bone-forming tissue. A decrease in the fibula growth rate has been observed in premature human infants given oral tetracycline in doses of 25 mg/kg every six hours. This reaction was shown to be reversible when the drug was discontinued.

Results of animal studies indicate that tetracyclines cross the placenta, are found in fetal tissues, and can have toxic effects on the developing fetus (often related to retardation of skeletal development). Evidence of embryotoxicity has been noted in animals treated early in pregnancy.

Drug Rash with Eosinophilia and Systemic Symptoms (DRESS) including fatal cases have been reported with minocycline use. Fixed drug eruptions have occurred with minocycline and other tetracyclines. Worsening severity upon subsequent administrations, including generalized bullous fixed drug eruption, has been observed with other tetracyclines (see ADVERSE REACTIONS). If severe skin reactions occur, discontinue minocycline hydrochloride tablets immediately and institute appropriate therapy.
The anti-anabolic action of the tetracyclines may cause an increase in BUN. While this is not a problem in those with normal renal function, in patients with significantly impaired function, higher serum levels of tetracycline may lead to azotemia, hyperphosphatemia, and acidosis. Under such conditions, monitoring of creatinine and BUN is recommended, and the total daily dosage should not exceed 200 mg in 24 hours (see DOSAGE AND ADMINISTRATION). If renal impairment exists, even usual oral or parenteral doses may lead to systemic accumulation of the drug and possible liver toxicity.

Photosensitivity manifested by an exaggerated sunburn reaction has been observed in some individuals taking tetracyclines. This has been reported with minocycline.

Central nervous system side effects including light-headedness, dizziness, or vertigo have been reported with minocycline therapy. Patients who experience these symptoms should be cautioned about driving vehicles or using hazardous machinery while on minocycline therapy. These symptoms may disappear during therapy and usually disappear rapidly when the drug is discontinued.

Clostridium difficile associated diarrhea (CDAD) has been reported with use of nearly all antibacterial agents, including minocycline hydrochloride, and may range in severity from mild diarrhea to fatal colitis. Treatment with antibacterial agents alters the normal flora of the colon leading to overgrowth of C. difficile.

C. difficile produces toxins A and B which contribute to the development of CDAD. Hypertoxin producing strains of C. difficile cause increased morbidity and mortality, as these infections can be refractory to antimicrobial therapy and may require colectomy. CDAD must be considered in all patients who present with diarrhea following antibiotic use. Careful medical history is necessary since CDAD has been reported to occur over two months after the administration of antibacterial agents.

If CDAD is suspected or confirmed, ongoing antibiotic use not directed against C. difficile may need to be discontinued. Appropriate fluid and electrolyte management, protein supplementation, antibiotic treatment of C. difficile, and surgical evaluation should be instituted as clinically indicated.

PRECAUTIONS

General

As with other antibiotic preparations, use of this drug may result in overgrowth of non-susceptible organisms, including fungi. If superinfection occurs, the antibiotic should be discontinued and appropriate therapy instituted.

Pseudotumor cerebri (benign intracranial hypertension) in adults has been associated with the use of tetracyclines. The usual clinical manifestations are headache and blurred vision. Bulging fontanels have been associated with the use of tetracyclines in infants. While both of these conditions and related symptoms usually resolve after discontinuation of the tetracycline, the possibility for permanent sequelae exists.

Hepatotoxicity has been reported with minocycline; therefore, minocycline should be used with caution in patients with hepatic dysfunction and in conjunction with other hepatotoxic drugs.

Incision and drainage or other surgical procedures should be performed in conjunction with antibiotic therapy when indicated.

Prescribing minocycline hydrochloride tablets in the absence of a proven or strongly suspected bacterial infection or a prophylactic indication is unlikely to provide benefit to the patient and increases the risk of the development of drug resistant bacteria.

Information For Patients

Diarrhea is a common problem caused by antibiotics which usually ends when the antibiotic is discontinued. Sometimes after starting treatment with antibiotics, patients can develop watery and bloody stools (with or without stomach cramps and fever) even as late as two or more months after having taken the last dose of the antibiotic. If this occurs, patients should contact their physician as soon as possible.

Photosensitivity manifested by an exaggerated sunburn reaction has been observed in some individuals taking tetracyclines. Patients apt to be exposed to direct sunlight or ultraviolet light should be advised that this reaction can occur with tetracycline drugs, and treatment should be discontinued at the first evidence of skin erythema. This reaction has been reported with use of minocycline.

Patients who experience central nervous system symptoms should be cautioned about driving vehicles or using hazardous machinery while on minocycline therapy (see WARNINGS).

Concurrent use of tetracycline with oral contraceptives may render oral contraceptives less effective (see Drug Interactions).

Patients should be counseled that antibacterial drugs including minocycline hydrochloride tablets should only be used to treat bacterial infections. They do not treat viral infections (e.g., the common cold). When minocycline hydrochloride tablets are prescribed to treat a bacterial infection, patients should be told that although it is common to feel better early in the course of therapy, the medication should be taken exactly as directed. Skipping doses or not completing the full course of therapy may: (1) decrease the effectiveness of the immediate treatment and (2) increase the likelihood that bacteria will develop resistance and will not be treatable by minocycline hydrochloride tablets or other antibacterial drugs in the future.

Unused supplies of tetracycline antibiotics should be discarded by the expiration date.

Laboratory Tests

In venereal disease when coexistent syphilis is suspected, a dark-field examination should be done before treatment is started and the blood serology repeated monthly for at least four months.

Periodic laboratory evaluations of organ systems, including hematopoietic, renal, and hepatic, should be performed.

Drug Interactions

Because tetracyclines have been shown to depress plasma prothrombin activity, patients who are on anticoagulant therapy may require downward adjustment of their anticoagulant dosage.

Since bacteriostatic drugs may interfere with the bactericidal action of penicillin, it is advisable to avoid giving tetracycline-class drugs in conjunction with penicillin.

Absorption of tetracyclines is impaired by antacids containing aluminum, calcium, or magnesium, and iron-containing preparations.

The concurrent use of tetracycline and methoxyflurane has been reported to result in fatal renal toxicity.

Concurrent use of tetracyclines with oral contraceptives may render oral contraceptives less effective.

Administration of isotretinoin should be avoided shortly before, during, and shortly after minocycline therapy. Each drug alone has been associated with pseudotumor cerebri (see PRECAUTIONS).

Increased risk of ergotism when ergot alkaloids or their derivatives are given with tetracyclines.

Drug/ Laboratory Test Interactions

False elevations of urinary catecholamine levels may occur due to interference with the fluorescence test.

Carcinogenesis, Mutagenesis, Impairment of Fertility

Dietary administration of minocycline in long term tumorigenicity studies in rats resulted in evidence of thyroid tumor production. Minocycline has also been found to produce thyroid hyperplasia in rats and dogs. In addition, there has been evidence of oncogenic activity in rats in studies with a related antibiotic, oxytetracycline (i.e., adrenal and pituitary tumors). Likewise, although mutagenicity studies of minocycline have not been conducted, positive results in in vitro mammalian cell assays (i.e., mouse lymphoma and Chinese hamster lung cells) have been reported for related antibiotics (tetracycline hydrochloride and oxytetracycline). Segment I (fertility and general reproduction) studies have provided evidence that minocycline impairs fertility in male rats.

Pregnancy

Teratogenic Effects: Pregnancy Category D (see WARNINGS).

All pregnancies have a background risk of birth defects, loss, or other adverse outcome regardless of drug exposure. There are no adequate and well-controlled studies on the use of minocycline in pregnant women. Minocycline, like other tetracycline-class antibiotics, crosses the placenta and may cause fetal harm when administered to a pregnant woman. Rare spontaneous reports of congenital anomalies including limb reduction have been reported in post-marketing experience. Only limited information is available regarding these reports; therefore, no conclusion on causal association can be established. If minocycline is used during pregnancy or if the patient becomes pregnant while taking this drug, the patient should be apprised of the potential hazard to the fetus.

Nonteratogenic Effects: (see WARNINGS).

Labor and Delivery

The effect of tetracyclines on labor and delivery is unknown.

Nursing Mothers

Tetracyclines are excreted in human milk. Because of the potential for serious adverse reactions in nursing infants from the tetracyclines, a decision should be made whether to discontinue nursing or discontinue the drug, taking into account the importance of the drug to the mother (see WARNINGS).

Pediatric Use

Minocycline is not recommended for use in children below 8 years of age unless the expected benefits of therapy outweigh the risks (see WARNINGS).

Geriatric Use

Clinical studies of oral minocycline did not include sufficient numbers of subjects aged 65 and over to determine whether they respond differently from younger subjects. In general, dose selection for an elderly patient should be cautious, usually starting at the low end of the dosing range, reflecting the greater frequency of decreased hepatic, renal, or cardiac function, and of concomitant disease or other drug therapy (see WARNINGS, DOSAGE AND ADMINISTRATION).

ADVERSE REACTIONS

Due to oral minocycline’s virtually complete absorption, side effects to the lower bowel, particularly diarrhea, have been infrequent. The following adverse reactions have been observed in patients receiving tetracyclines.

Body as a whole: Fever, and discoloration of secretions.

Gastrointestinal: Anorexia, nausea, vomiting, diarrhea, dyspepsia, stomatitis, glossitis, dysphagia, enamel hypoplasia, enterocolitis, pseudomembranous colitis, pancreatitis, inflammatory lesions (with monilial overgrowth) in the oral and anogenital regions. Instances of esophagitis and esophageal ulcerations have been reported in patients taking the tetracycline-class antibiotics in capsule and tablet form. Most of these patients took the medication immediately before going to bed (see DOSAGE AND ADMINISTRATION).

Genitourinary: Vulvovaginitis.

Hepatic toxicity: Hyperbilirubinemia, hepatic cholestasis, increases in liver enzymes, fatal hepatic failure, and jaundice. Hepatitis, including autoimmune hepatitis, and liver failure have been reported (see PRECAUTIONS).

Skin: Alopecia, erythema nodosum, hyperpigmentation of nails, pruritus, toxic epidermal necrolysis, and vasculitis. Maculopapular and erythematous rashes. Exfoliative dermatitis has been reported. Fixed drug eruptions have been reported. Lesions occurring on the glans penis have caused balanitis. Erythema multiforme and Stevens-Johnson syndrome have been reported. Photosensitivity is discussed above (see WARNINGS). Pigmentation of the skin and mucous membranes has been reported.

Respiratory: Cough, dyspnea, bronchospasm, exacerbation of asthma, and pneumonitis.

Renal toxicity: Interstitial nephritis. Elevations in BUN have been reported and are apparently dose related (see WARNINGS). Reversible acute renal failure has been reported.

Musculoskeletal: Arthralgia, arthritis, bone discoloration, myalgia, joint stiffness, and joint swelling.

Hypersensitivity reactions: Urticaria, angioneurotic edema, polyarthralgia, anaphylaxis/anaphylactoid reaction (including shock and fatalities), anaphylactoid purpura, myocarditis, pericarditis, exacerbation of systemic lupus erythematosus and pulmonary infiltrates with eosinophilia have been reported. A transient lupus-like syndrome and serum sickness-like reactions have also been reported.

Blood: Agranulocytosis, hemolytic anemia, thrombocytopenia, leukopenia, neutropenia, pancytopenia, and eosinophilia have been reported.

Central Nervous System: Convulsions, dizziness, hypesthesia, paresthesia, sedation, and vertigo. Bulging fontanels in infants and benign intracranial hypertension (pseudotumor cerebri) in adults have been reported (see PRECAUTIONS-General). Headache has also been reported.

Other: Thyroid cancer has been reported in the post-marketing setting in association with minocycline products. When minocycline therapy is given over prolonged periods, monitoring for signs of thyroid cancer should be considered. When given over prolonged periods, tetracyclines have been reported to produce brown-black microscopic discoloration of the thyroid gland. Cases of abnormal thyroid function have been reported.

Tooth discoloration in children less than 8 years of age, and also in adults, has been reported (see WARNINGS).

Oral cavity discoloration (including tongue, lip, and gum) have been reported.

Tinnitus and decreased hearing have been reported in patients on minocycline hydrochloride.

The following syndromes have been reported. In some cases involving these syndromes, death has been reported. As with other serious adverse reactions, if any of these syndromes are recognized, the drug should be discontinued immediately:

Hypersensitivity syndrome consisting of cutaneous reaction (such as rash or exfoliative dermatitis), eosinophilia, and one or more of the following: hepatitis, pneumonitis, nephritis, myocarditis, and pericarditis. Fever and lymphadenopathy may be present.

Lupus-like syndrome consisting of positive antinuclear antibody; arthralgia, arthritis, joint stiffness, or joint swelling; and one or more of the following: fever, myalgia, hepatitis, rash, and vasculitis.

Serum sickness-like syndrome consisting of fever; urticaria or rash; and arthralgia, arthritis, joint stiffness, or joint swelling. Eosinophilia may be present.

OVERDOSAGE

The adverse events more commonly seen in overdose are dizziness, nausea, and vomiting.

No specific antidote for minocycline is known.

In case of overdosage, discontinue medication, treat symptomatically and institute supportive measures. Minocycline is not removed in significant quantities by hemodialysis or peritoneal dialysis.

DOSAGE AND ADMINISTRATION

THE USUAL DOSAGE AND FREQUENCY OF ADMINISTRATION OF MINOCYCLINE DIFFERS FROM THAT OF THE OTHER TETRACYCLINES. EXCEEDING THE RECOMMENDED DOSAGE MAY RESULT IN AN INCREASED INCIDENCE OF SIDE EFFECTS.

Minocycline hydrochloride tablets may be taken with or without food (see CLINICAL PHARMACOLOGY).

Ingestion of adequate amounts of fluids along with capsule and tablet forms of drugs in the tetracycline-class is recommended to reduce the risk of esophageal irritation and ulceration. The tablets should be swallowed whole.

For Pediatric Patients Above 8 Years of Age

Usual pediatric dose: 4 mg/kg initially followed by 2 mg/kg every 12 hours, not to exceed the usual adult dose.

Adults

The usual dosage of minocycline hydrochloride tablets is 200 mg initially followed by 100 mg every 12 hours. Alternatively, if more frequent doses are preferred, two or four 50 mg tablets may be given initially followed by one 50 mg tablet four times daily.

Uncomplicated gonococcal infections other than urethritis and anorectal infections in men: 200 mg initially, followed by 100 mg every 12 hours for a minimum of four days, with post-therapy cultures within 2 to 3 days.

In the treatment of uncomplicated gonococcal urethritis in men, 100 mg every 12 hours for 5 days is recommended.

For the treatment of syphilis, the usual dosage of minocycline hydrochloride should be administered over a period of 10 to 15 days. Close follow-up, including laboratory tests, is recommended.

In the treatment of meningococcal carrier state, the recommended dosage is 100 mg every 12 hours for five days.

Mycobacterium marinum infections: Although optimal doses have not been established, 100 mg every 12 hours for 6 to 8 weeks have been used successfully in a limited number of cases.

Uncomplicated urethral, endocervical, or rectal infection in adults caused by Chlamydia trachomatis or Ureaplasma urealyticum: 100 mg orally, every 12 hours for at least seven days.

Ingestion of adequate amounts of fluids along with capsule and tablet forms of drugs in the tetracycline-class is recommended to reduce the risk of esophageal irritation and ulceration.

The pharmacokinetics of minocycline in patients with renal impairment (CLCR <80mL/min) have not been fully characterized. Current data are insufficient to determine if a dosage adjustment is warranted. The total daily dosage should not exceed 200 mg in 24 hours. However, due to the anti-anabolic effect of tetracyclines, BUN and creatinine should be monitored (see WARNINGS).

HOW SUPPLIED

Minocycline hydrochloride tablets, USP are supplied as aqueous film-coated tablets containing minocycline hydrochloride USP equivalent to 50 mg, 75 mg and 100 mg minocycline.

Minocycline Hydrochloride Tablets, USP 50 mg are white, unscored, modified capsule shaped, coated tablet debossed with “50” on one side and “M” on the other side. Each tablet contains minocycline hydrochloride USP equivalent to 50 mg minocycline, supplied as follows:

Bottle of 100 NDC 59651-337-01

Minocycline Hydrochloride Tablets, USP 75 mg are white, unscored, modified capsule shaped, coated tablet debossed with “75” on one side and “M” on the other side. Each tablet contains minocycline hydrochloride USP equivalent to 75 mg minocycline, supplied as follows:

Bottle of 100 NDC 59651-338-01

Minocycline Hydrochloride Tablets, USP 100 mg are white, unscored, modified capsule shaped, coated tablet debossed with “100” on one side and “M” on the other side. Each tablet contains minocycline hydrochloride USP equivalent to 100 mg minocycline, supplied as follows:

Bottle of 50 NDC 59651-339-50

Store at 20 to 25ºC (68º to 77ºF) [See USP Controlled Room Temperature]

Protect from light, moisture, and excessive heat.

Dispense in a tight, light-resistant container as defined in the USP.

ANIMAL PHARMACOLOGY AND TOXICOLOGY

Minocycline hydrochloride has been observed to cause a dark discoloration of the thyroid in experimental animals (rats, minipigs, dogs and monkeys). In the rat, chronic treatment with minocycline hydrochloride has resulted in goiter accompanied by elevated radioactive iodine uptake and evidence of thyroid tumor production. Minocycline hydrochloride has also been found to produce thyroid hyperplasia in rats and dogs.

PATIENT INFORMATION

Minocycline Hydrochloride

(min’’ oh sye’ kleen hye’’ droe klor’ ide)

Tablets, USP

50 mg, 75 mg, and 100 mg

Read the Patient Information that comes with minocycline hydrochloride tablets before you or a family member starts taking it and each time you get a refill. There may be new information. This leaflet does not take the place of talking to your doctor about your medical condition or treatment.

What are minocycline hydrochloride tablets?

Minocycline hydrochloride tablets are a tetracycline-class antibiotic medicine. Minocycline hydrochloride tablets are used to treat certain infections caused by bacteria. These include infections of the skin, respiratory tract, urinary tract, some sexually transmitted diseases, and others. Minocycline hydrochloride tablets may be used along with other treatments for severe acne.

Sometimes, other germs, called viruses cause infections. The common cold is a virus. Minocycline hydrochloride tablets, like other antibiotics, does not treat viruses.

Who should not use minocycline hydrochloride tablets?

Do not take minocycline hydrochloride tablets if you are allergic to minocycline or other tetracycline antibiotics.

Ask your doctor or pharmacist for a list of these medications if you are not sure. See the end of this leaflet for a complete list of ingredients in minocycline hydrochloride tablets.

Minocycline hydrochloride tablets are not recommended for pregnant women or children up to 8 years old because:

1. Minocycline hydrochloride tablets may harm an unborn baby.

2. Minocycline hydrochloride tablets may permanently turn a baby’s or child’s teeth yellow-gray-brown during tooth development. Tooth development happens in the last half of pregnancy and birth to age 8 years.
What should I tell my doctor before starting minocycline hydrochloride tablets?

Tell your doctor about all of your medical conditions, including if you:

- have liver or kidney problems.

- are pregnant or planning to become pregnant. Minocycline hydrochloride tablets may harm your unborn baby. Stop taking minocycline hydrochloride tablets and call your doctor if you become pregnant while taking it.
- are breast feeding. Minocycline hydrochloride passes into your milk and may harm your baby. You should decide whether to use minocycline hydrochloride tablets or breastfeed, but not both.

Tell your doctor about all the medicines you are taking including prescription and non- prescription medications, vitamins, and herbal supplements. Minocycline hydrochloride tablets and other medicines may interact. Especially tell your doctor if you take:

- birth control pills. Minocycline hydrochloride tablets may make your birth control pills less effective.
- a blood thinner medicine. The dose of your blood thinner may have to be lowered.
- a penicillin antibiotic medicine. Minocycline hydrochloride tablets and penicillins should not be used together.
- Migraine medicines called ergot alkaloids.
- An acne medicine called isotretinoin (Accutane®, Amnesteem®, Claravis®, Sotret®).
- Antacids that contain aluminum, calcium, or magnesium, or iron-containing products.

Know the medicines you take, keep a list of them to show your doctor and pharmacist each time you get a new medicine.

How should I take minocycline hydrochloride tablets?

- Take minocycline hydrochloride tablets exactly as your doctor tells you to take them. Skipping doses or not taking all your minocycline hydrochloride tablets may:

- Decrease the effectiveness of the treatment.
- Increase the chance that bacteria will develop resistance to minocycline hydrochloride.

- Take minocycline hydrochloride tablets with a full glass of liquid. Taking minocycline hydrochloride tablets with enough liquid may lower your chance of getting irritation or ulcers in your esophagus. Your esophagus is the tube that connects your mouth to your stomach.
- Minocycline hydrochloride tablets may be taken with or without food. If you forget to take minocycline hydrochloride tablets, take it as soon as you remember.
- If you take too much minocycline hydrochloride, call you doctor or poison control center right away.

What are the possible side effects of minocycline hydrochloride tablets?

Minocycline hydrochloride tablets may cause serious side effects. Stop minocycline hydrochloride tablets and call your doctor if you have:

- watery diarrhea
- bloody stools
- stomach cramps
- unusual headaches
- blurred vision
- fever
- rash
- joint pain
- feeling very tired

Minocycline hydrochloride tablets may also cause:

- central nervous system effects. Symptoms include light-headedness, dizziness, and a spinning feeling (vertigo). You should not drive or operate machines if you have these symptoms.

- sun sensitivity (photosensitivity). You may get a worse sunburn with minocycline hydrochloride tablets. Avoid sun exposure and the use of sunlamps or tanning beds. Protect your skin while out in the sunlight. Stop minocycline hydrochloride tablets and call your doctor if your skin turns red.

These are not all the side effects with minocycline hydrochloride tablets. Ask your doctor or pharmacist for more information.

How should I store minocycline hydrochloride Tablets?

- Store minocycline hydrochloride tablets at room temperature and away from excess heat and moisture.

- Throw away any minocycline hydrochloride tablets that is outdated or no longer needed.
- Keep minocycline hydrochloride tablets and all medicines out of the reach of children.

General advice about minocycline hydrochloride Tablets

Medicines are sometimes prescribed for purposes other than those listed in a Patient Information leaflet. Do not use minocycline hydrochloride tablets for a condition for which it was not prescribed. Do not give minocycline hydrochloride tablets to other people, even if they have the same symptoms you have. It may harm them.

This Patient Information leaflet summarizes the most important information about minocycline hydrochloride tablets. If you would like more information, talk with your doctor.

Your doctor or pharmacist can give you information about minocycline hydrochloride tablets that is written for health care professionals. For more information, you can also call Aurobindo Pharma USA, Inc. at 1-866-850-2876.

What are the ingredients in minocycline hydrochloride tablets?

Active ingredient: minocycline hydrochloride, 50 mg, 75 mg, and 100 mg

Inactive ingredients: colloidal silicon dioxide, hypromellose, lactose monohydrate, magnesium stearate, microcrystalline cellulose, polyethylene glycol, polysorbate 80, povidone, sodium starch glycolate and titanium dioxide.

All trademarks are the property of their respective owners.

Distributed by:
Aurobindo Pharma USA, Inc.
279 Princeton-Hightstown Road
East Windsor, NJ 08520
Manufactured by:
Aurobindo Pharma Limited
Hyderabad-500 032, India
Revised: 01/2025

PACKAGE LABEL-PRINCIPAL DISPLAY PANEL - 50 mg (100 Tablets Bottle)

NDC 59651-337-01
Minocycline Hydrochloride
Tablets, USP
50 mg
Rx only 100 Tablets
AUROBINDO

PACKAGE LABEL-PRINCIPAL DISPLAY PANEL - 75 mg (100 Tablets Bottle)

NDC 59651-338-01
Minocycline Hydrochloride
Tablets, USP
75 mg
Rx only 100 Tablets
AUROBINDO

PACKAGE LABEL-PRINCIPAL DISPLAY PANEL - 100 mg (50 Tablets Bottle)

NDC 59651-339-50
Minocycline Hydrochloride
Tablets, USP
100 mg
Rx only 50 Tablets
AUROBINDO